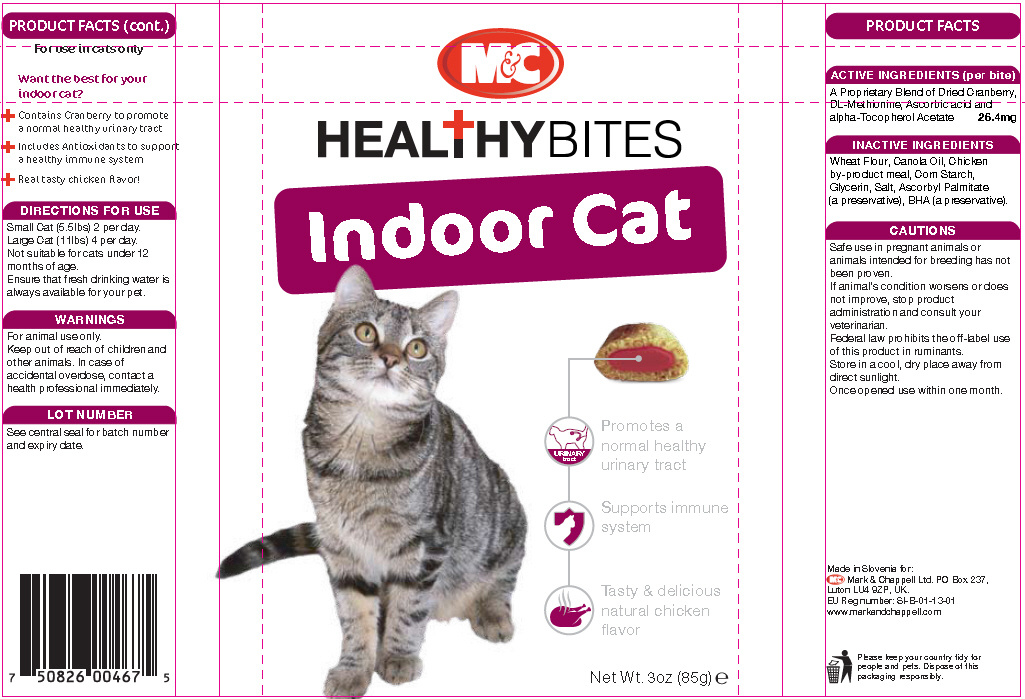 DRUG LABEL: Healthy Bites Indoor Cat
								
								
NDC: 28689-467 | Form: PELLET
Manufacturer: Mark and Chappell Ltd
Category: animal | Type: OTC ANIMAL DRUG LABEL
Date: 20130614

ACTIVE INGREDIENTS: Cranberry .0195 g/.65 g; N-Acetylmethionine, DL- .0065 g/.65 g; Ascorbic Acid .0004 g/.65 g; Alpha-Tocopherol Acetate .000036 g/.65 g
INACTIVE INGREDIENTS: Wheat; Canola Oil; Chicken; Starch, Corn; Glycerin; Sodium Chloride; Ascorbyl Palmitate; Butylated Hydroxyanisole

ACTIVE INGREDIENTS (per bite)

A Proprietary Blend of Dried Cranberry, DL-Methionine, Ascorbic Acid and alpha-Tocopherol Actetate 26.4mg

INACTIVE INGREDIENTS

Wheat Flour, Canola Oil, Chicken by-product meal, Corn Starch, Glycerin, Salt, Ascorbyl Palmitate (a preservative), BHA (a preservative)

GENERAL PRECAUTIONS

CAUTIONS

Safe use in pregnant animals or animals intended for breeding has not been proven.
If animal's condition worsens or does not improve, stop product administration and consult your veterinarian.
Federal law prohibits the off-label use of this product in ruminants.
Store in cool, dry place away from direct sunlight.
Once opened use within one month.

For use in cats only.

DESCRIPTION

Want the best for your indoor cat?

- Contains cranberry to promote a normal healthy urinary tract
- Includes antioxidants to support a healthy immune system
- Real tasty chicken flavor!

DIRECTIONS FOR USE

Small Cats (5.5 lbs) 2 per day.
Large Cats (11 lbs) 4 per day.

Not suitable for cats under 12 months of age.
Ensure that fresh drinking water is always available for your pet.

WARNINGS

For animal use only.
Keep out of reach of children and other animals. In case of accidental overdose, contact a health professional immediately.

PACKAGE LABEL

Healthy Bites Indoor Cat

Net Wt 3oz (85g) e